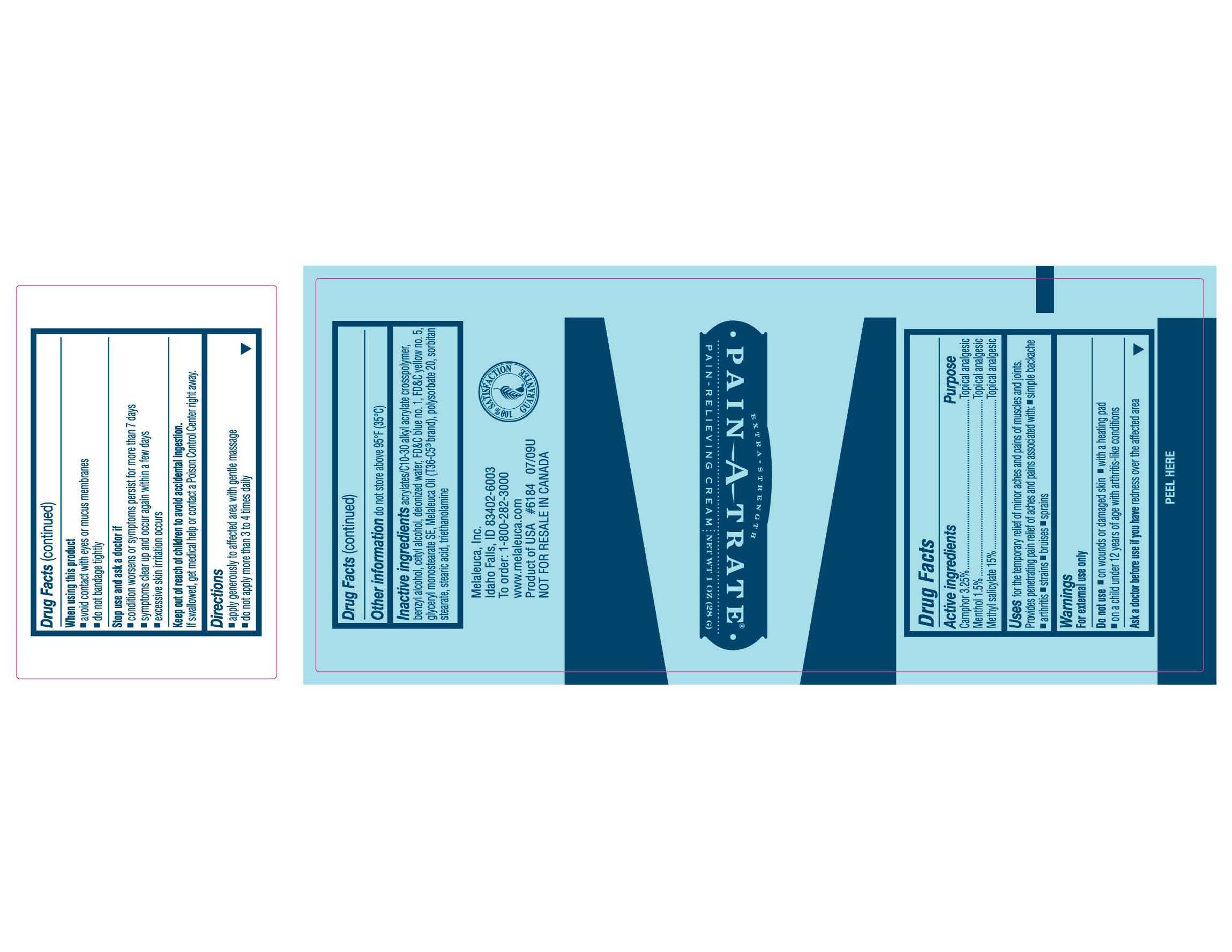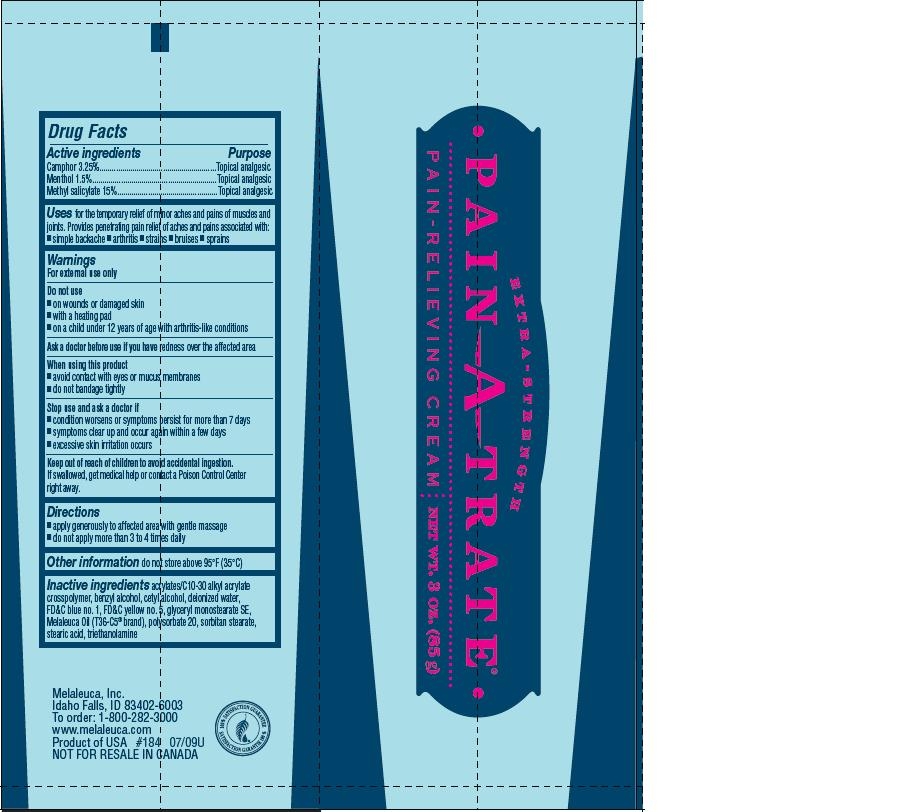 DRUG LABEL: Pain-A-Trate
NDC: 54473-150 | Form: CREAM
Manufacturer: Melaleuca, Inc.
Category: otc | Type: HUMAN OTC DRUG LABEL
Date: 20200319

ACTIVE INGREDIENTS: CAMPHOR (SYNTHETIC) 32.5 mg/1 g; MENTHOL 15 mg/1 g; METHYL SALICYLATE 150 mg/1 g
INACTIVE INGREDIENTS: WATER; GLYCERYL MONOSTEARATE; STEARIC ACID; CETYL ALCOHOL; SORBITAN MONOSTEARATE; POLYSORBATE 20; TEA TREE OIL; TROLAMINE; CARBOMER COPOLYMER TYPE B; BENZYL ALCOHOL; FD&C BLUE NO. 1; FD&C YELLOW NO. 5

Pain-A-Trate Extra Strength Pain-Relieving Cream

Active ingredients
Camphor 3.25%
Menthol, 1.5%
Methyl Salicylate, 15%

Purpose
Topical analgesic

INDICATIONS AND USAGE

Uses for the temporary relief of minor aches and pains of muscles and joints. Provides penetrating pain relief of aches and pains associated with:

- simple backache
- arthritis
- strains
- bruises
- sprains

Warnings
For external use only

Do not use

- on wounds or damaged skin
- with a heating pad
- on a child under 12 years of age with arthritis-like conditions

Ask a doctor before use if you have redness over the affected area.

When using this product

- avoid contact with eyes or mucus membranes
- do not bandage tightly

Stop use and ask a doctor if

- condition worsens or symptoms persist for more than 7 days
- excessive skin irritation occurs

Keep out of reach of children to avoid accidental ingestion. If swallowed, get medical help or contact a Poison Control Center right away.

Directions

- apply generously to affected area with gentle massage
- do not apply more than 3 to 4 times daily

Other information do not store above 95°F (35°C)

INACTIVE INGREDIENT

Inactive ingredients acrylates/C10-30 alkyl acrylate crosspolymer, benzyl alcohol, cetyl alcohol, deionized water, FD and C blue no. 1, FD and C yellow no. 5, glyceryl monostearate SE, Melaleuca Oil (T36-C5® brand), polysorbate 20, sorbitan stearate, steric acid, triethanolamine